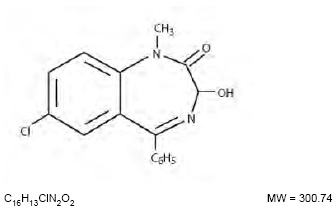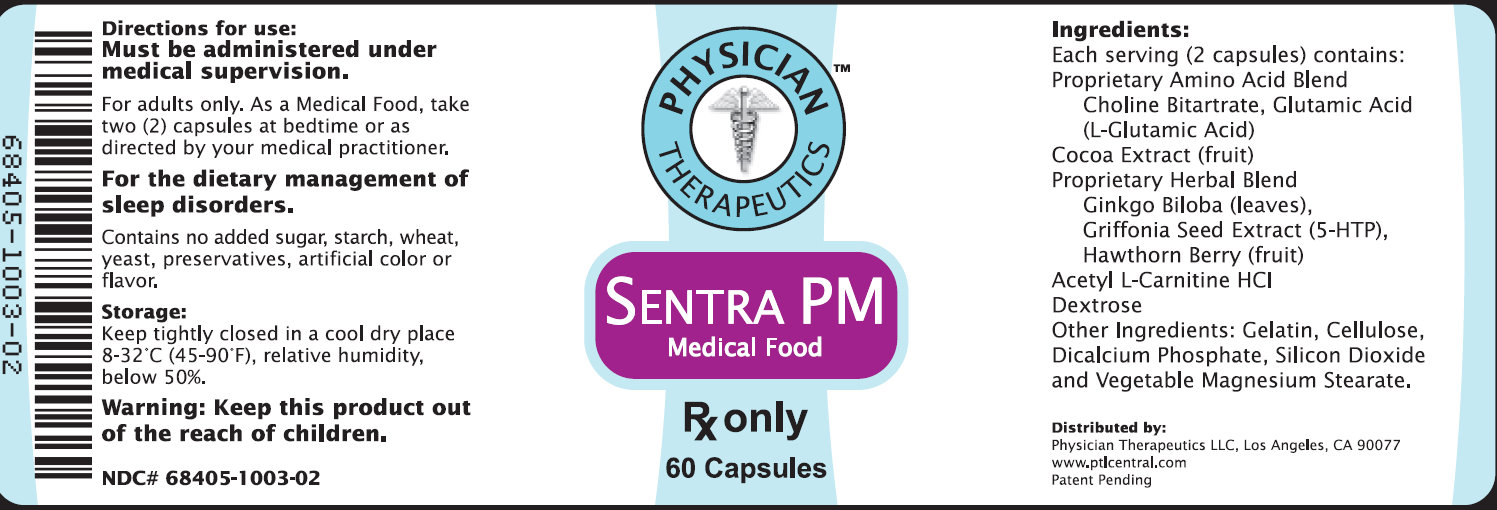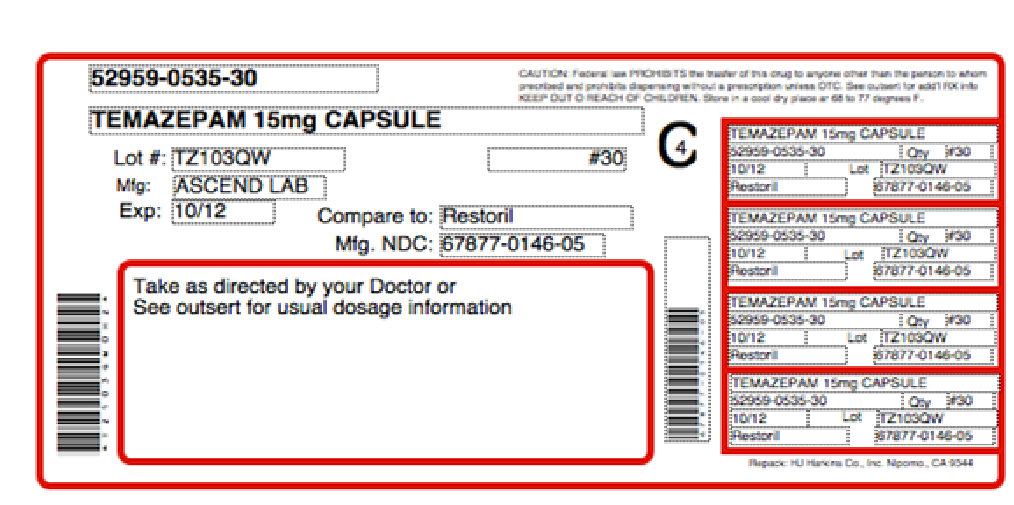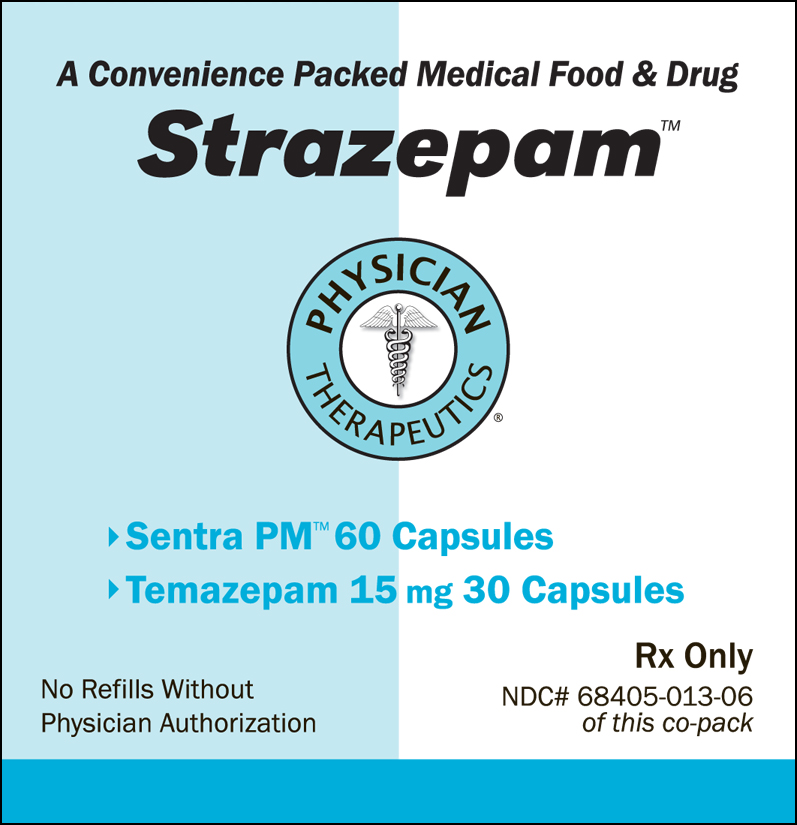 DRUG LABEL: Strazepam
NDC: 68405-013 | Form: KIT | Route: ORAL
Manufacturer: Physician Therapeutics LLC
Category: prescription | Type: HUMAN PRESCRIPTION DRUG LABEL
Date: 20110801

ACTIVE INGREDIENTS: TEMAZEPAM 15 mg/1 1; CHOLINE 250 mg/1 1
INACTIVE INGREDIENTS: STARCH, CORN; ANHYDROUS LACTOSE; MAGNESIUM STEARATE; SODIUM LAURYL SULFATE; FD&C BLUE NO. 1; FD&C YELLOW NO. 6; GELATIN; TITANIUM DIOXIDE; SODIUM LAURYL SULFATE; AMMONIA; ALCOHOL; ISOPROPYL ALCOHOL; BUTYL ALCOHOL; SHELLAC; POTASSIUM HYDROXIDE; PROPYLENE GLYCOL; FERROSOFERRIC OXIDE; MAGNESIUM STEARATE; CELLULOSE, MICROCRYSTALLINE; MALTODEXTRIN; GELATIN

Strazepam

DESCRIPTION

DESCRIPTION Temazepam is a benzodiazepine hypnotic agent. The chemical name is 7-chloro 1,3-dihydro-3-hydroxyl-methyl-5-phenyl-2H-1,4-benzodiazepin-2-one, and the structural formula is:

Temazepam is a white, crystalline substance, very slightly soluble in water and sparingly soluble in alcohol USP. Temazepam capsules, 15 mg and 30 mg, are for oral administration. 15 mg and 30 mg Capsules Active Ingredient: temazepam USP 15 mg Capsules Inactive Ingredients: Corn starch, lactose anhydrous, magnesium stearate, sodium lauryl sulfate, FDandC Blue #1, FDandC yellow # 5, FDandC yellow # 6, gelatin and titanium dioxide.

May also include: benzyl alcohol, butylparaben, sodium lauryl sulfate, edetate calcium disodium, methylparaben, propyl paraben and sodium propionate. Imprinting ink may contain ammonium hydroxide, ethanol, 2-propanol, butanol, pharmaceutical shellac, potassium hydroxide, propylene glycol, black iron oxide, and other ingredents. 30 mg Capsules Inactive Ingredients: Corn starch, lactose anhydrous, magnesium stearate, sodium lauryl sulfate, gelatin and titanium dioxide. May also include: benzyl alcohol, butylparaben, sodium lauryl sulfate, edetate calcium disodium, methylparaben, propyl paraben and sodium propionate. Imprinting ink may contain ammonium hydroxide, ethanol, 2-propanol, butanol, pharmaceutical shellac, potassium hydroxide, propylene glycol, black iron oxide, and other ingredents. Structural Formula

PHARMACOKINETICS

CLINICAL PHARMACOLOGY Pharmacokinetics In a single and multiple dose absorption, distribution, metabolism, and excretion (ADME) study, using 3H labeled drug, temazepam was well absorbed and found to have minimal (8%) first pass metabolism. There were no active metabolites formed and the only significant metabolite present in blood was the O-conjugate. The unchanged drug was 96% bound to plasma proteins. The blood level decline of the parent drug was biphasic with the short half-life ranging from 0.4 to 0.6 hours and the terminal half-life from 3.5 to 18.4 hours (mean 8.8 hours), depending on the study population and method of determination. Metabolites were formed with a half-life of 10 hours and excreted with a half-life of approximately 2 hours. Thus, formation of the major metabolite is the rate limiting step in the biodisposition of temazepam. There is no accumulation of metabolites. A dose-proportional relationship has been established for the area under the plasma concentration/time curve over the 15 to 30 mg dose range. Temazepam was completely metabolized through conjugation prior to excretion; 80% to 90% of the dose appeared in the urine. The major metabolite was the O-conjugate of temazepam (90%); the O-conjugate of N-desmethyl temazepam was a minor metabolite (7%). Bioavailability, Induction, and Plasma Levels Following ingestion of a 30 mg temazepam capsule, measurable plasma concentrations were achieved 10 to 20 minutes after dosing with peak plasma levels ranging from 666 to 982 ng/mL (mean 865 ng/mL) occurring approximately 1.2 to 1.6 hours (mean 1.5 hours) after dosing. In a 7 day study, in which subjects were given a 30 mg temazepam capsule 1 hour before retiring, steady-state (as measured by the attainment of maximal trough concentrations) was achieved by the third dose. Mean plasma levels of temazepam (for days 2 to 7) were 260±210 ng/mL at 9 hours and 75±80 ng/mL at 24 hours after dosing. A slight trend toward declining 24 hour plasma levels was seen after day 4 in the study, however, the 24 hour plasma levels were quite variable. At a dose of 30 mg once-a-day for 8 weeks, no evidence of enzyme induction was found in man.

Elimination Rate of Benzodiazepine Hypnotics and Profile of Common Untoward Effects The type and duration of hypnotic effects and the profile of unwanted effects during administration of benzodiazepine hypnotics may be influenced by the biologic half-life of the administered drug and for some hypnotics, the half-life of any active metabolites formed. Benzodiazepine hypnotics have a spectrum of half-lives from short (4 hours) to long (20 hours). When half-lives are long, drug (and for some drugs their active metabolites) may accumulate during periods of nightly administration and be associated with impairments of cognitive and/or motor performance during waking hours; the possibility of interaction with other psychoactive drugs or alcohol will be enhanced. In contrast, if half-lives are shorter, drug (and, where appropriate, its active metabolites) will be cleared before the next dose is ingested, and carry-over effects related to excessive sedation or CNS depression should be minimal or absent. However, during nightly use for an extended period, pharmacodynamic tolerance or adaptation to some effects of benzodiazepine hypnotics may develop. If the drug has a short elimination half-life, it is possible that a relative deficiency of the drug, or, if appropriate, its active metabolites (i.e., in relationship to the receptor site) may occur at some point in the interval between each night's use. This sequence of events may account for 2 clinical findings reported to occur after several weeks of nightly use of rapidly eliminated benzodiazepine hypnotics, namely, increased wakefulness during the last third of the night, and the appearance of increased signs of daytime anxiety. Controlled Trials Supporting Efficacy Temazepam improved sleep parameters in clinical studies. Residual medication effects ("hangover") were essentially absent. Early morning awakening, a particular problem in the geriatric patient, was significantly reduced. Patients with chronic insomnia were evaluated in 2 week, placebo controlled sleep laboratory studies with temazepam at doses of 7.5 mg, 15 mg, and 30 mg, given 30 minutes prior to bedtime.

There was a linear dose-response improvement in total sleep time and sleep latency, with significant drug-placebo differences at 2 weeks occurring only for total sleep time at the 2 higher doses, and for sleep latency only at the highest dose. In these sleep laboratory studies, REM sleep was essentially unchanged and slow wave sleep was decreased. No measurable effects on daytime alertness or performance occurred following temazepam treatment or during the withdrawal period, even though a transient sleep disturbance in some sleep parameters was observed following withdrawal of the higher doses. There was no evidence of tolerance development in the sleep laboratory parameters when patients were given temazepam nightly for at least 2 weeks. In addition, normal subjects with transient insomnia associated with first night adaptation to the sleep laboratory were evaluated in 24 hour, placebo controlled sleep laboratory studies with temazepam at doses of 7.5 mg, 15 mg, and 30 mg, given 30 minutes prior to bedtime. There was a linear doseresponse improvement in total sleep time, sleep latency and number of awakenings, with significant drug-placebo differences occurring for sleep latency at all doses, for total sleep time at the 2 higher doses and for number of awakenings only at the 30 mg dose.

INDICATIONS AND USAGE Temazepam Capsules, USP are indicated for the short-term treatment of insomnia (generally 7 to 10 days). For patients with short-term insomnia, instructions in the prescription should indicate that Temazepam Capsules should be used for short periods of time (7 to 10 days). The clinical trials performed in support of efficacy were 2 weeks in duration with the final formal assessment of sleep latency performed at the end of treatment.

CONTRAINDICATIONS

CONTRAINDICATIONS Benzodiazepines may cause fetal harm when administered to a pregnant woman. An increased risk of congenital malformations associated with the use of diazepam and chlordiazepoxide during the first trimester of pregnancy has been suggested in several studies. Transplacental distribution has resulted in neonatal CNS depression following the ingestion of therapeutic doses of a benzodiazepine hypnotic during the last weeks of pregnancy. Reproduction studies in animals with temazepam were performed in rats and rabbits. In a perinatalpostnatal study in rats, oral doses of 60 mg/kg/day resulted in increasing nursling mortality. Teratology studies in rats demonstrated increased fetal resorptions at doses of 30 and 120 mg/kg in one study and increased occurrence of rudimentary ribs, which are considered skeletal variants, in a second study at doses of 240 mg/kg or higher. In rabbits, occasional abnormalities such as exencephaly and fusion or asymmetry of ribs were reported without dose relationship. Although these abnormalities were not found in the concurrent control group, they have been reported to occur randomly in historical controls. At doses of 40 mg/kg or higher, there was an increased incidence of the 13th rib variant when compared to the incidence in concurrent and historical controls.

Temazepam is contraindicated in women who are or may become pregnant. If this drug is used during pregnancy, or if the patient becomes pregnant while taking this drug, the patient should be apprised of the potential hazard to the fetus. Patients should be instructed to discontinue the drug prior to becoming pregnant. The possibility that a woman of childbearing potential may be pregnant at the time of institution of therapy should be considered.

WARNINGS

WARNINGS Sleep disturbance may be the presenting manifestation of an underlying physical and/or psychiatric disorder. Consequently, a decision to initiate symptomatic treatment of insomnia should only be made after the patient has been carefully evaluated. The failure of insomnia to remit after 7 to 10 days of treatment may indicate the presence of a primary psychiatric and/or medical illness that should be evaluated. Worsening of insomnia may be the consequence of an unrecognized psychiatric or physical disorder as may the emergence of new abnormalities of thinking or behavior. Such abnormalities have also been reported to occur in association with the use of drugs with central nervous system depressant activity, including those of the benzodiazepine class. Because some of the worrisome adverse effects of benzodiazepines, including temazepam, appear to be dose related (see PRECAUTIONS and DOSAGE AND ADMINISTRATION), it is important to use the lowest possible effective dose. Elderly patients are especially at risk. Some of these changes may be characterized by decreased inhibition, e.g., aggressiveness and extroversion that seem out of character, similar to that seen with alcohol. Other kinds of behavioral changes can also occur, for example, bizarre behavior, agitation, hallucinations, and depersonalization. Complex behaviors such as "sleepdriving" (i.e., driving while not fully awake after ingestion of a sedativehypnotic, with amnesia for the event) have been reported. These events can occur in sedativehypnoticnaive as well as in sedative-hypnotic-experienced persons.

Although behaviors such as sleep-driving may occur with temazepam alone at therapeutic doses, the use of alcohol and other CNS depressants with temazepam appears to increase the risk of such behaviors, as does the use of temazepam at doses exceeding the maximum recommended dose. Due to the risk to the patient and the community, discontinuation of temazepam should be strongly considered for patients who report a "sleep-driving" episode. Other complex behaviors (e.g., preparing and eating food, making phone calls, or having sex) have been reported in patients who are not fully awake after taking a sedative-hypnotic. As with sleepdriving, patients usually do not remember these events. Amnesia and other neuro-psychiatric symptoms may occur unpredictably. In primarily depressed patients, worsening of depression, including suicidal thinking has been reported in association with the use of sedative/hypnotics. It can rarely be determined with certainty whether a particular instance of the abnormal behaviors listed above is drug induced, spontaneous in origin, or a result of an underlying psychiatric or physical disorder. Nonetheless, the emergence of any new behavioral sign or symptom of concern requires careful and immediate evaluation. Withdrawal symptoms (of the barbiturate type) have occurred after the abrupt discontinuation of benzodiazepines (see DRUG ABUSE AND DEPENDENCE).

Severe Anaphylactic and Anaphylactoid Reactions Rare cases of angioedema involving the tongue, glottis or larynx have been reported in patients after taking the first or subsequent doses of sedative-hypnotics, including temazepam. Some patients have had additional symptoms such as dyspnea, throat closing, or nausea and vomiting that suggest anaphylaxis. Some patients have required medical therapy in the emergency department. If angioedema involves the tongue, glottis or larynx, airway obstruction may occur and be fatal. Patients who develop angioedema after treatment with temazepam should not be rechallenged with the drug.

PRECAUTIONS

PRECAUTIONS General Since the risk of the development of oversedation, dizziness, confusion, and/or ataxia increases substantially with larger doses of benzodiazepines in elderly and debilitated patients, 7.5 mg of temazepam is recommended as the initial dosage for such patients. Temazepam should be administered with caution in severely depressed patients or those in whom there is any evidence of latent depression; it should be recognized that suicidal tendencies may be present and protective measures may be necessary. The usual precautions should be observed in patients with impaired renal or hepatic function and in patients with chronic pulmonary insufficiency. If temazepam is to be combined with other drugs having known hypnotic properties or CNS-depressant; and effects, consideration should be given to potential additive effects. The possibility of a synergistic effect exists with the co-administration of temazepam and diphenhydramine. One case of stillbirth at term has been reported 8 hours after a pregnant patient received temazepam and diphenhydramine. A cause and effect relationship has not yet been determined (see CONTRAINDICATIONS).

PATIENT COUNSELING INFORMATION

Information for Patients The text of a patient Medication Guide is printed at the end of this insert. To assure safe and effective use of temazepam, the information and instructions provided in this patient Medication Guide should be discussed with patients. Special Concerns "Sleep-Driving" and Other Complex Behaviors - There have been reports of people getting out of bed after taking a sedative-hypnotic and driving their cars while not fully awake, often with no memory of the event. If a patient experiences such an episode, it should be reported to his or her doctor immediately, since "sleep-driving" can be dangerous. This behavior is more likely to occur when temazepam is taken with alcohol or other central nervous system depressants (see WARNINGS). Other complex behaviors (e.g., preparing and eating food, making phone calls, or having sex) have been reported in patients who are not fully awake after taking a sedative-hypnotic. As with sleep-driving, patients usually do not remember these events.

LABORATORY TESTS

Laboratory Test The usual precautions should be observed in patients with impaired renal or hepatic function and in patients with chronic pulmonary insufficiency. Abnormal liver function tests as well as blood dyscrasias have been reported with benzodiazepines.

DRUG INTERACTIONS

Drug Interactions The pharmacokinetic profile of temazepam does not appear to be altered by orally administered cimetidine dosed according to labeling.

CARCINOGENESIS AND MUTAGENESIS AND IMPAIRMENT OF FERTILITY

Carcinogenesis, Mutagenesis, Impairment of Fertility Carcinogenicity studies were conducted in rats at dietary temazepam doses up to 160 mg/kg/day for 24 months and in mice at dietary doses of 160 mg/kg/day for 18 months. No evidence of carcinogenicity was observed although hyperplastic liver nodules were observed in female mice exposed to the highest dose. The clinical significance of this finding is not known.

Fertility in male and female rats was not adversely affected by temazepam. No mutagenicity tests have been done with temazepam.

Pregnancy Pregnancy Category X (see CONTRAINDICATIONS).

NURSING MOTHERS

Nursing Mothers It is not known whether this drug is excreted in human milk. Because many drugs are excreted in human milk, caution should be exercised when temazepam is administered to a nursing woman.

PEDIATRIC USE

Pediatric Use Safety and effectiveness in pediatric patients have not been established.

ADVERSE REACTIONS

ADVERSE REACTIONS During controlled clinical studies in which 1076 patients received temazepam at bedtime, the drug was well tolerated. Side effects were usually mild and transient. Adverse reactions occurring in 1% or more of patients are presented in the following table:

 | Temazepam % Incidence (n=1076) | Placebo % Incidence (n=783)
Drowsiness | 9.1 | 5.6
Headache | 8.5 | 9.1
Fatigue | 4.8 | 4.7
Nervousness | 4.6 | 8.2
Lethargy | 4.5 | 3.4
Dizziness | 4.5 | 3.3
Nausea | 3.1 | 3.8
Hangover | 2.5 | 1.1
Anxiety | 2.0 | 1.5
Depression | 1.7 | 1.8
Dry Mouth | 1.7 | 2.2
Diarrhea | 1.7 | 1.1
Abdominal Discomfort | 1.5 | 1.9
Euphoria | 1.5 | 0.4
Weakness | 1.4 | 0.9
Confusion | 1.3 | 0.5
Blurred Vision | 1.3 | 1.3
Nightmares | 1.2 | 1.7
Vertigo | 1.2 | 0.8

The following adverse events have been reported less frequently (0.5% to 0.9%): Central Nervous System - anorexia, ataxia, equilibrium loss, tremor, increased dreaming Cardiovascular - dyspnea, palpitations Gastrointestinal – vomiting Musculoskeletal – backache Special Senses - hyperhidrosis, burning eyes Amnesia, hallucinations, horizontal nystagmus, and paradoxical reactions including restlessness, overstimulation and agitation were rare (less than 0.5%).

DRUG ABUSE AND DEPENDENCE Abuse and addiction are separate and distinct from physical dependence and tolerance. Abuse is characterized by misuse of the drug for non-medical purposes, often in combination with other psychoactive substances. Physical dependence is a state of adaptation that is manifested by a specific withdrawal syndrome that can be produced by abrupt cessation, rapid dose reduction, decreasing blood level of the drug and/or administration of an antagonist. Tolerance is a state of adaptation in which exposure to a drug induces changes that result in a diminution of one or more of the drug's effects over time. Tolerance may occur to both the desired and undesired effects of drugs and may develop at different rates for different effects. Addiction is a primary, chronic, neurobiological disease with genetic, psychosocial, and environmental factors influencing its development and manifestations. It is characterized by behaviors that include one or more of the following: impaired control over drug use, compulsive use, continued use despite harm, and craving. Drug addiction is a treatable disease, utilizing a multidisciplinary approach, but relapse is common.

CONTROLLED SUBSTANCE

Controlled Substance Temazepam is a controlled substance in Schedule IV.

ABUSE

Abuse and Dependence Withdrawal symptoms, similar in character to those noted with barbiturates and alcohol (convulsions, tremor, abdominal, and muscle cramps, vomiting, and sweating), have occurred following abrupt discontinuance of benzodiazepines. The more severe withdrawal symptoms have usually been limited to those patients who received excessive doses over an extended period of time. Generally milder withdrawal symptoms (e.g., dysphoria and insomnia) have been reported following abrupt discontinuance of benzodiazepines taken continuously at therapeutic levels for several months. Consequently, after extended therapy at doses higher than 15 mg, abrupt discontinuation should generally be avoided and a gradual dosage tapering schedule followed. As with any hypnotic, caution must be exercised in administering temazepam to individuals known to be addiction-prone or to those whose history suggests they may increase the dosage on their own initiative. It is desirable to limit repeated prescriptions without adequate medical supervision.

OVERDOSAGE

Manifestations of acute overdosage of temazepam can be expected to reflect the CNS effects of the drug and include somnolence, confusion, and coma, with reduced or absent reflexes, respiratory depression, and hypotension. The oral LD50 of temazepam was 1963 mg/kg in mice, 1833 mg/kg in rats, and >2400 mg/kg in rabbits.

Treatment If the patient is conscious, vomiting should be induced mechanically or with emetics. Gastric lavage should be employed utilizing concurrently a cuffed endotracheal tube if the patient is unconscious to prevent aspiration and pulmonary complications. Maintenance of adequate pulmonary ventilation is essential. The use of pressor agents intravenously may be necessary to combat hypotension. Fluids should be administered intravenously to encourage diuresis. The value of dialysis has not been determined. If excitation occurs, barbiturates should not be used. It should be borne in mind that multiple agents may have been ingested. Flumazenil (Romazicorn®)*, a specific benzodiazepine receptor antagonist, is indicated for the complete or partial reversal of the sedative effects of benzodiazepines and may be used in situations when an overdose with a benzodiazepine is known or suspected. Prior to the administration of flumazenil, necessary measures should be instituted to secure airway, ventilation, and intravenous access. Flumazenil is intended as an adjunct to, not as a substitute for, proper management of benzodiazepine overdose. Patients treated with flumazenil should be monitored for re-sedation, respiratory depression, and other residual benzodiazepine effects for an appropriate period after treatment. The prescriber should be aware of a risk of seizure in association with flumazenil treatment, particularly in long-term benzodiazepine users and in cyclic antidepressant overdose. The complete flumazenil package insert including CONTRAINDICATIONS, WARNINGS, and PRECAUTIONS should be consulted prior to use. Up-to-date information about the treatment of overdose can often be obtained from a certified Regional Poison Control Center. Telephone numbers of certified Regional Poison Control Centers are listed in the Physicians’ Desk References®**

DOSAGE AND ADMINISTRATION While the recommended usual adult dose is 15 mg before retiring, 7.5 mg may be sufficient for some patients, and others may need 30 mg. In transient insomnia, a 7.5 mg dose may be sufficient to improve sleep latency. In elderly or debilitated patients, it is recommended that therapy be initiated with 7.5 mg until individual responses are determined.

HOW SUPPLIED

HOW SUPPLIED Temazepam Capsules USP 15 mg Green opaque cap and white opaque body, imprinted “15 mg” on cap and “Novel 121” on the body in black ink.

Bottle of 100........NDC 67877-146-01
Bottle of 500........NDC 67877-146-05

30 mg White opaque cap and body, imprinted “30 mg” on cap and “Novel 123” on the body in black ink.
Bottle of 100........NDC 67877-147-01
Bottle of 500........NDC 67877-147-05

Dispense in a well-closed, light-resistant container with a child-resistant closure.

*Romazicon is the registered trademark of Hoffman-LaRoche Inc.

**Trademark of Medical Economics Company, Inc.

Manufactured by:

Distributed by: Novel Laboratories, Inc.

ASCEND Laboratories, LLC Somerset, NJ 08873

Montvale, NJ 07645

STORAGE AND HANDLING

Storage: Store at 20° to 25°C (68° to 77°F) [see USP Controlled Room Temperature].

MEDICATION GUIDE

MEDICATION GUIDE TEMAZEPAM Capsules, USP C-IV (temazepam) Read the Medication Guide that comes with TEMAZEPAM before you start taking it and each time you get a refill. There may be new information. This Medication Guide does not take the place of talking to your doctor about your medical condition or treatment.

____________________________________________________________________

What is the most important information I should know about TEMAZEPAM? After taking TEMAZEPAM, you may get up out of bed while not being fully awake and do an activity that you do not know you are doing. The next morning, you may not remember that you did anything during the night. You have a higher chance for doing these activities if you drink alcohol or take other medicines that make you sleepy with TEMAZEPAM. Reported activities include: • driving a car ("sleep-driving") • making and eating food • talking on the phone • having sex • sleep-walking Call your doctor right away if you find out that you have done any of the above activities after taking TEMAZEPAM. Important: 1. Take TEMAZEPAM exactly as prescribed • Do not take more TEMAZEPAM than prescribed. • Take TEMAZEPAM right before you get in bed, not sooner. 2. Do not take TEMAZEPAM if you: • drink alcohol • take other medicines that can make you sleepy. Talk to your doctor about all of your medicines. Your doctor will tell you if you can take TEMAZEPAM with your other medicines • cannot get a full night's sleep

____________________________________________________________________

What is TEMAZEPAM? TEMAZEPAM is a sedative-hypnotic (sleep) medicine. TEMAZEPAM is used in adults for the short-term (usually 7 to 10 days) treatment of a sleep problem called insomnia.

Symptoms of insomnia include: • trouble falling asleep • waking up often during the night TEMAZEPAM is not for children. TEMAZEPAM is a federally controlled substance (C-IV) because it can be abused or lead to dependence. Keep TEMAZEPAM in a safe place to prevent misuse and abuse. Selling or giving away TEMAZEPAM may harm others, and is against the law. Tell your doctor if you have ever abused or been dependent on alcohol, prescription medicines or street drugs.

Who should not take TEMAZEPAM?

Do not take TEMAZEPAM if you are pregnant or planning to become pregnant. TEMAZEPAM may cause birth defects or harm a fetus (unborn baby). TEMAZEPAM may not be right for you. Before starting TEMAZEPAM, tell your doctor about all of your health conditions, including if you:
• have a history of depression, mental illness, or suicidal • have a history of drug or alcohol abuse or addiction
• have kidney or liver disease
• have a lung disease or breathing problems
• are breastfeeding Tell your doctor about all of the medicines you take including prescription and nonprescription medicines, vitamins and herbal supplements. Medicines can interact with each other, sometimes causing serious side effects. Do not take TEMAZEPAM with other medicines that can make you sleepy. Know the medicines you take. Keep a list of your medicines with you to show your doctor and pharmacist each time you get a new medicine. How should I take TEMAZEPAM? • Take TEMAZEPAM exactly as prescribed. Do not take more TEMAZEPAM than prescribed for you.

• Take TEMAZEPAM right before you get into bed.
• Do not take TEMAZEPAM unless you are able to get a full night's sleep before you must be active again.
• Call your doctor if your insomnia worsens or is not better within 7 to 10 days. This may mean that there is another condition causing your sleep problems.
• If you take too much TEMAZEPAM or overdose, call your doctor or poison control center right away, or get emergency treatment. What are the possible side effects of TEMAZEPAM? Possible serious side effects of TEMAZEPAM include:
• getting out of bed while not being fully awake and do an activity that you do not know you are doing. (See "What is the most important information I should know about TEMAZEPAM?")
• abnormal thoughts and behavior. Symptoms include more outgoing or aggressive behavior than normal, confusion, agitation, hallucinations, worsening of depression, and suicidal thoughts.
• memory loss
• anxiety
• severe allergic reactions. Symptoms include swelling of the tongue or throat, trouble breathing, and nausea and vomiting. Get emergency medical help if you get these symptoms after taking TEMAZEPAM. Call your doctor right away if you have any of the above side effects or any other side effects that worry you while using TEMAZEPAM.

The most common side effects of TEMAZEPAM are:
• drowsiness
• headache
• tiredness
• nervousness
• dizziness
• nausea
• "hangover" feeling the day after taking TEMAZEPAM

You may still feel drowsy the next day after taking TEMAZEPAM. Do not drive or do other dangerous activities after taking TEMAZEPAM until you feel fully awake. You may have withdrawal symptoms if you stop taking TEMAZEPAM suddenly. Withdrawal symptoms can be serious and include seizures. Mild withdrawal symptoms include a depressed mood and trouble sleeping. Talk to your doctor to check if you need to stop TEMAZEPAM slowly. These are not all the side effects of TEMAZEPAM. Ask your doctor or pharmacist for more information. How should I store TEMAZEPAM? • Store TEMAZEPAM at room temperature, 68° to 77°F (20° to 25°C). • Keep TEMAZEPAM and all medicines out of reach of children. General Information about TEMAZEPAM

Medicines are sometimes prescribed for purposes other than those listed in a Medication Guide.

Do not use TEMAZEPAM for a condition for which it was not prescribed.

Do not share TEMAZEPAM with other people, even if you think they have the same symptoms that you have. It may harm them and it is against the law. This Medication Guide summarizes the most important information about TEMAZEPAM. If you would like more information, talk with your doctor. You can ask your doctor or pharmacist for information about TEMAZEPAM that is written for healthcare professionals. What are the ingredients in TEMAZEPAM? TEMAZEPAM is a federally controlled substance (C-IV) because it can be abused or lead to dependence. Keep TEMAZEPAM in a safe place to prevent misuse and abuse. Selling or giving away TEMAZEPAM may harm others, and is against the law. Tell your doctor if you have ever abused or been dependent on alcohol, prescription medicines or street drugs. 15mg and 30mg Capsules

Active Ingredient: temazepam USP 15 mg Capsules

Inactive Ingredients: Corn starch, lactose anhydrous, magnesium stearate, sodium lauryl sulfate, FDandC Blue #1, FDandC yellow # 5, FDandC yellow # 6, gelatin and titanium dioxide. May also include: benzyl alcohol ,butylparaben, sodium lauryl sulfate, edetate calcium disodium, methylparaben, propyl paraben and sodium propionate. Imprinting ink may contain ammonium hydroxide, ethanol, 2-propanol, butanol, pharmaceutical shellac, potassium hydroxide, propylene glycol, black iron oxide, and other ingredents. 30 mg Capsules Inactive Ingredients: Corn starch, lactose anhydrous, magnesium stearate, sodium lauryl sulfate, gelatin and titanium dioxide. May also include: benzyl alcohol ,butylparaben, sodium lauryl sulfate, edetate calcium disodium, methylparaben, propyl paraben and sodium propionate. Imprinting ink may contain ammonium hydroxide, ethanol, 2-propanol, butanol, pharmaceutical shellac, potassium hydroxide, propylene glycol, black iron oxide, and other ingredents.

Manufactured by: Novel Laboratories, Inc Somerset, NJ 08873

Distributed by: ASCEND Laboratories, LLC Montvale, NJ 07645

ALPI-147-05-00 Rev: 06/09

ASCEND Laboratories, LLC NDC 67877-146-01

TEMAZEPAM CIV Capsules, USP

15 mg

Rx only

100 capsules

INACTIVE INGREDIENT

INGREDIENTS

Name | Type | Strength | Moiety | UNII | Preferred Substance
temazepam | Active | 15 mg In 1 | temazepam | CHB1QD2QSS | TEMAZEPAM
starch, corn | Inactive |  |  | O8232NY3SJ | STARCH, CORN
anhydrous lactose | Inactive |  |  | 3SY5LH9PMK | ANHYDROUS LACTOSE
magnesium stearate | Inactive |  |  | 70097M6I30 | MAGNESIUM STEARATE
sodium lauryl sulfate | Inactive |  |  | 368GB5141J | SODIUM LAURYL SULFATE
FDandC BLUE NO. 1 | Inactive |  |  | H3R47K3TBD | FDandC BLUE NO. 1
FDandC YELLOW NO. 5 | Inactive |  |  | I753WB2F1M | FDandC YELLOW NO. 5
FDandC YELLOW NO. 6 | Inactive |  |  | H77VEI93A8 | FDandC YELLOW NO. 6
gelatin | Inactive |  |  | 2G86QN327L | GELATIN
titanium dioxide | Inactive |  |  | 15FIX9V2JP | TITANIUM DIOXIDE
benzyl alcohol | Inactive |  |  | LKG8494WBH | BENZYL ALCOHOL
butylparaben | Inactive |  |  | 3QPI1U3FV8 | BUTYLPARABEN
sodium lauryl sulfate | Inactive |  |  | 368GB5141J | SODIUM LAURYL SULFATE
edetate calcium disodium | Inactive |  |  | 25IH6R4SGF | EDETATE CALCIUM DISODIUM
methylparaben | Inactive |  |  | A2I8C7HI9T | METHYLPARABEN
propylparaben | Inactive |  |  | Z8IX2SC1OH | PROPYLPARABEN
sodium propionate | Inactive |  |  | DK6Y9P42IN | SODIUM PROPIONATE
ammonia | Inactive |  |  | 5138Q19F1X | AMMONIA
alcohol | Inactive |  |  | 3K9958V90M | ALCOHOL
isopropyl alcohol | Inactive |  |  | ND2M416302 | ISOPROPYL ALCOHOL
butyl alcohol | Inactive |  |  | 8PJ61P6TS3 | BUTYL ALCOHOL
shellac | Inactive |  |  | 46N107B71O | SHELLAC
potassium hydroxide | Inactive |  |  | WZH3C48M4T | POTASSIUM HYDROXIDE
propylene glycol | Inactive |  |  | 6DC9Q167V3 | PROPYLENE GLYCOL
ferrosoferric oxide | Inactive |  |  | XM0M87F357 | FERROSOFERRIC OXIDE

PACKAGE LABEL

Packaged by Bryant Ranch

North Hollywood CA 91605

Temazepam 15mg(CIV)

Capsule Compare to Restore 15mg(CIV)

Capsule

MYLAN PHARMACEUTICALS NC #30

EXP 11/09 NDC 6362916192 NANA LOT 10973

Rx Only

Do Not Drink Alcohol

May Cause Drowsiness/No Alcohol

Sentra PM™PRODUCT INFORMATION
Sentra PM (U.S. patent pending) capsules by oral administration. A specially formulated Medical Food product, consisting of a proprietary blend of amino acids and polyphenol ingredients in specific proportions, for the dietary management of the metabolic processes of sleep disorders (SD). Must be administered under physician supervision.
Medical Foods Medical Food products are often used in hospitals (e.g., for burn victims or kidney dialysis patients) and outside of a hospital setting under a physician’s care for the dietary management of diseases in patients with particular medical or metabolic needs due to their disease or condition. Congress defined "Medical Food" in the Orphan Drug Act and Amendments of 1988 as "a system which is formulated to be consumed or administered enterally [or orally] under the supervision of a physician and which is intended for the specific dietary management of a disease or condition for which distinctive nutritional requirements, based on recognized scientific principles, are established by medical evaluation." Medical Foods are complex formulated products, requiring sophisticated and exacting technology. Sentra PM has been developed, manufactured, and labeled in accordance with both the statutory and the FDA regulatory definition of a Medical Food. Sentra PM must be used while the patient is under the ongoing care of a physician.
SLEEP DISORDERS (SD)
SD as a Metabolic Deficiency Disease A critical component of the definition of a Medical Food is the requirement for a distinctive nutritional deficiency. FDA scientists have proposed a physiologic definition of a distinctive nutritional deficiency as follows: “the dietary management of patients with specific diseases requires, in some instances, the ability to meet nutritional requirements that differ substantially from the needs of healthy persons. For example, in establishing the recommended dietary allowances for general, healthy population, the Food and Nutrition Board of the Institute of Medicine National Academy of Sciences, recognized that different or distinctive physiologic requirements may exist for certain persons with "special nutritional needs arising from metabolic disorders, chronic diseases, injuries, premature birth, other medical conditions and drug therapies. Thus, the distinctive nutritional needs associated with a disease reflect the total amount needed by a healthy person to support life or maintain homeostasis, adjusted for the distinctive changes in the nutritional needs of the patient as a result of the effects of the disease process on absorption, metabolism, and excretion.” It was also proposed that in patients with certain disease states who respond to nutritional therapies, a physiologic deficiency of the nutrient is assumed to exist. For example, if a patient with sleep disorders responds to a tryptophan formulation by improving the duration and quality of sleep, a deficiency of tryptophan is assumed to exist.
Patients with sleep disorders are known to have nutritional deficiencies of tryptophan, choline, flavonoids, and certain antioxidants. Patients with sleep disorders frequently exhibit reduced plasma levels of tryptophan and have been shown to respond to oral administration of tryptophan or a 5-hydoxytryptophan formulation. Research has shown that tryptophan reduced diets result in a fall of circulating tryptophan. Patients with sleep disorders have activation of the tryptophan degradation pathway that increases the turnover of tryptophan leading to a reduced level of production of serotonin for a given tryptophan blood level. Research has also shown that a genetic predisposition can lead to increased tryptophan requirements in certain patients with sleep disorders.
Choline is required to fully potentiate acetylcholine synthesis by brain neurons. A deficiency of choline leads to reduced acetylcholine production by the neurons. Low fat diets, frequently used by patients with sleep disorders, are usually choline deficient. Flavonoids potentiate the production of acetylcholine by the neurons thereby inducing REM sleep. Low fat diets and diets deficient in flavonoid rich foods result in inadequate flavonoid concentrations, impeding acetylcholine production in certain patients with sleep disorders. Provision of tryptophan, choline, and flavonoids with antioxidants, in specific proportions can restore the production of beneficial serotonin and acetylcholine, thereby improving sleep quality.

PRODUCT DESCRIPTION
Primary Ingredients
Sentra PM consists of a proprietary blend of amino acids, cocoa, ginkgo biloba and flavonoids in specific proportions. These ingredients fall into the category of “Generally Regarded as Safe” (GRAS) as defined by the Food and Drug Administration (FDA) (Sections 201(s) and 409 of the Federal Food, Drug, and Cosmetic Act). A GRAS substance is distinguished from a food additive on the basis of the common knowledge about the safety of the substance for its intended use. The standard for an ingredient to achieve GRAS status requires not only technical demonstration of non-toxicity and safety, but also general recognition of safety through widespread usage and agreement of that safety by experts in the field. Many ingredients have been determined by the U.S. Food and Drug Administration (FDA) to be GRAS, and are listed as such by regulation, in Volume 21 Code of Federal Regulations (CFR) Sections 182, 184, and 186.
Amino Acids
Amino Acids are the building blocks of protein. All amino acids are GRAS listed as they have been ingested by humans for thousands of years. The doses of the amino acids in Sentra PM are equivalent to those found in the usual human diet; however the formulation uses specific ratios of the key ingredients to elicit a therapeutic response. Patients with sleep disorders may require an increased amount of certain amino acids that cannot be obtained from normal diet alone. Tryptophan, for example, is an obligatory amino acid. The body cannot make tryptophan and must obtain tryptophan from the diet. Tryptophan is needed to produce serotonin. Serotonin is required to induce sleep. Patients with sleep disorders have altered serotonin metabolism. Some patients with sleep disorders have a resistance to the use of tryptophan that is similar to the mechanism found in insulin resistance that is genetically determined. Patients with sleep disorders frequently cannot acquire sufficient tryptophan from the diet without ingesting a prohibitively large amount of calories, particularly protein rich calories.
Flavonoids
Flavonoids are a group of phytochemical compounds found in all vascular plants including fruits and vegetables. They are a part of a larger class of compounds known as polyphenols. Many of the therapeutic or health benefits of colored fruits and vegetables, cocoa, red wine, and green tea are directly related to their flavonoid content. The specially formulated flavonoids found in Sentra PM cannot be obtained from conventional foods in the necessary proportions to elicit a therapeutic response.
Other Ingredients
Sentra PM contains the following inactive or other ingredients, as fillers, excipients, and colorings: magnesium stearate, microcrystalline cellulose, Maltodextrin NF, gelatin (as the capsule material).
Physical Description
Sentra PM is a yellow to light brown powder. Sentra PM contains L-Glutamic Acid, 5-Hydroxytryptophan as Griffonia Seed Extract, Acetylcarnitine HCL, Choline Bitartrate, Cinnamon, Cocoa, Ginkgo Biloba, and Hawthorn Berry.

CLINICAL PHARMACOLOGY
Mechanism of Action
Sentra PM acts by restoring and maintaining the balance of the neurotransmitters, serotonin and acetylcholine, that are associated with sleep disorders.
Metabolism
The amino acids in Sentra PM are primarily absorbed by the stomach and small intestines. All cells metabolize the amino acids in Sentra PM. Circulating tryptophan and choline blood levels determine the production of serotonin and acetylcholine.
Excretion
Sentra PM is not an inhibitor of cytochrome P450 1A2, 2C9, 2C19, 2D6, or 3A4. These isoenzymes are principally responsible for 95% of all detoxification of drugs, with CYP3A4 being responsible for detoxification of roughly 50% of drugs. Amino acids do not appear to have an effect on drug metabolizing enzymes.

INDICATIONS FOR USE
Sentra PM is intended for the clinical dietary management of the metabolic processes associated with sleep disorders.

CLINICAL EXPERIENCE
The administration of Sentra PM has demonstrated significant functional improvement in the quality and quantity of sleep when used for the dietary management of the metabolic processes associated with sleep disorders. Administration of Sentra PM results in the induction and maintenance of sleep in patients with sleep disorders. Sentra PM has no effect on normal blood pressure.

PRECAUTIONS AND CONTRAINDICATIONS
Sentra PM is contraindicated in an extremely small number of patients with hypersensitivity to any of the nutritional components of Sentra PM.

ADVERSE REACTIONS
Oral supplementation with L-tryptophan or choline at high doses up to 15 grams daily is generally well tolerated. The most common adverse reactions of higher doses — from 15 to 30 grams daily — are nausea, abdominal cramps, and diarrhea. Some patients may experience these symptoms at lower doses. The total combined amount of amino acids in each Sentra PM capsule does not exceed 400 mg.

DRUG INTERACTIONS
Sentra PM does not directly influence the pharmacokinetics of prescription drugs. Clinical experience has shown that administration of Sentra PM may allow for lowering the dose of co-administered drugs under physician supervision.

OVERDOSAGE

OVERDOSE
There is a negligible risk of overdose with Sentra PM as the total dosage of amino acids in a one month supply (60 capsules) is less than 24 grams. Overdose symptoms may include diarrhea, weakness, and nausea.
POST-MARKETING SURVEILLANCE
Post-marketing surveillance has shown no serious adverse reactions. Reported cases of mild rash and itching may have been associated with allergies to Sentra PM flavonoid ingredients, including cinnamon, cocoa, and chocolate. The reactions were transient in nature and subsided within 24 hours.

DOSAGE AND ADMINISTRATION
Recommended Administration For the dietary management of the metabolic processes associated with sleep disorders. Take (2) capsules daily at bedtime. An additional dose of one or two capsules may be taken after awakenings during the night. As with most amino acid formulations Sentra PM should be taken without food to increase the absorption of key ingredients.

How Supplied
Sentra PM is supplied in red and white, size 0 capsules in bottles of 60 capsules.
Physician Supervision
Sentra PM is a Medical Food product available by prescription only and must be used while the patient is under ongoing physician supervision.
Sentra PM is supplied to physicians in a recyclable plastic bottle with a child-resistant cap.
U.S. patents pending.
Manufactured by Arizona Nutritional Supplements, Inc. Chandler AZ 85225
Distributed by Physician Therapeutics LLC, Los Angeles, CA 90077. www.ptlcentral.com
© Copyright 2003-2006, Physician Therapeutics LLC, all rights reserved
NDC # 68405-1003-02

Storage
Store at room temperature, 59-86OF (15-30OC). Protect from light and moisture.

MICROBIOLOGY

PHYSICIAN THERAPEUTICS SENTRA PM Medical Food Rx only 60 Capsules Directions for use: Must be administered under medical supervision. For adults only. As a Medical Food, take two (2) capsules at bedtime or as directed by your medical practitioner. For the dietary management of sleep disorders. Contains no added sugar, starch, wheat, yeast, preservatives, artificial color or flavor. Storage: Keep tightly closed in a cool dry place 8-320 C (45-900F), relative humidity, below 50%. Warning: Keep this product out of the reach of children. NDC# 68405-1003-02 Ingredients: Each serving (2 capsules) contains: Proprietary Amino Acid blend Choline Bitartrate, Glutamic Acid (L-Glutamic Acid), Cocoa Extract (fruit), Proprietary Herbal Blend Ginkgo Biloba (leaves), Griffonia Seed Extract (5-HTP), Hawthorn Berry (fruit), Acetyl L-Carnitine HCl, Dextrose Other Ingredients: Gelatin, Cellulose, Dicalcium Phosphate, Silicon Dioxide and Vegetable Magnesium Stearate.
Distributed by: Physician Therapeutics LLC, Los Angeles, CA 90077 www.ptlcentral.com Patent Pending

PACKAGE LABEL

A Convenience Packed Medical Food and Drug Strazepam PHYSICIAN THERAPEUTICS Sentra PM 60 Capsules Temazepam 15 mg 30 Capsules No Refills Without Physician Authorization Rx Only NDC# 68405-8013-06 of this co-pack For the Dietary Management of Sleep Disorders. Two capsules at bedtime or as directed by physician. See product label and insert. Sentra PM Medical Food As prescribed by physician. See product label and product information insert. Temazepam 15mg Rx Drug Physician Therapeutics LLC Los Angeles, CA 90077 on November 21, 2006